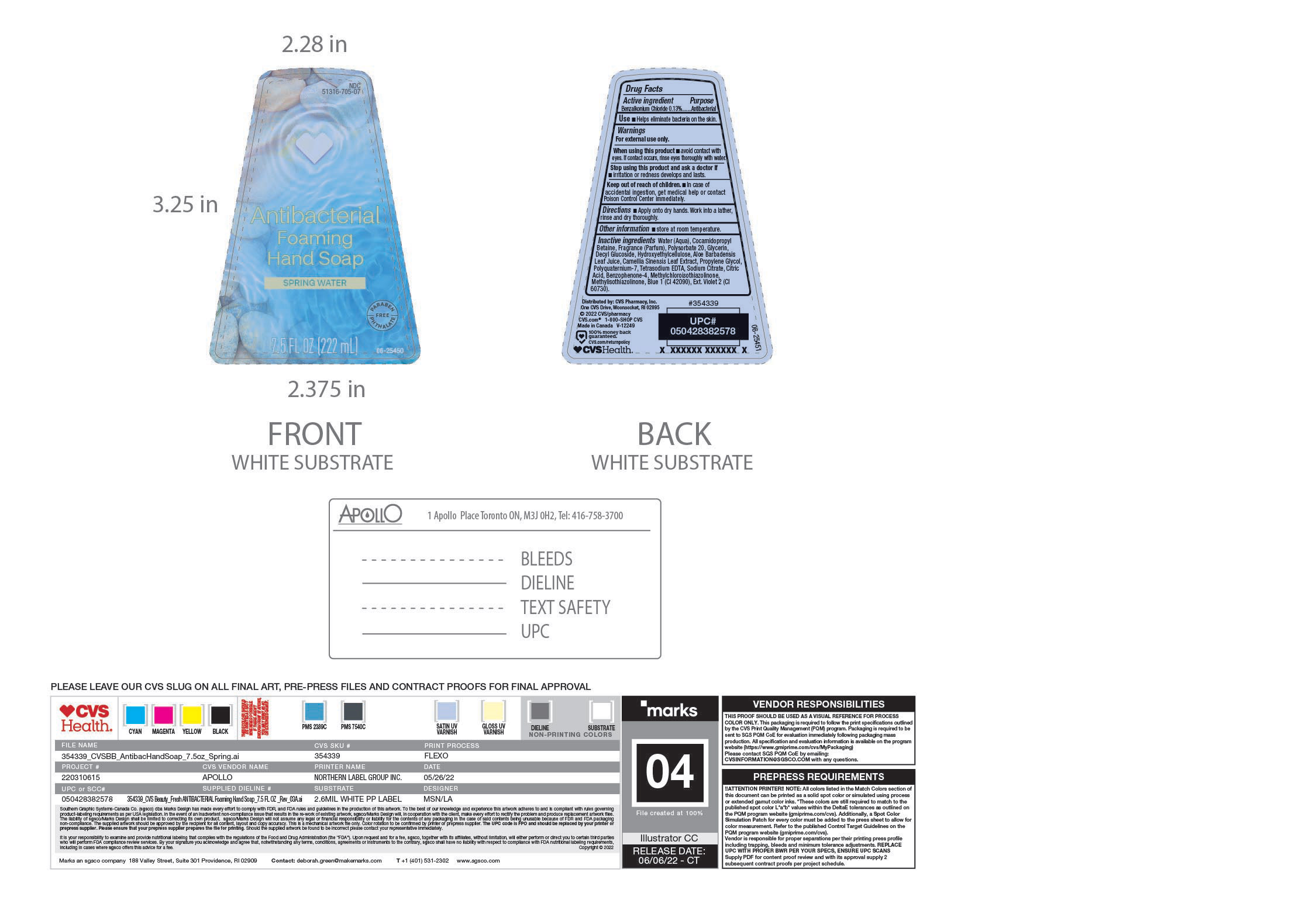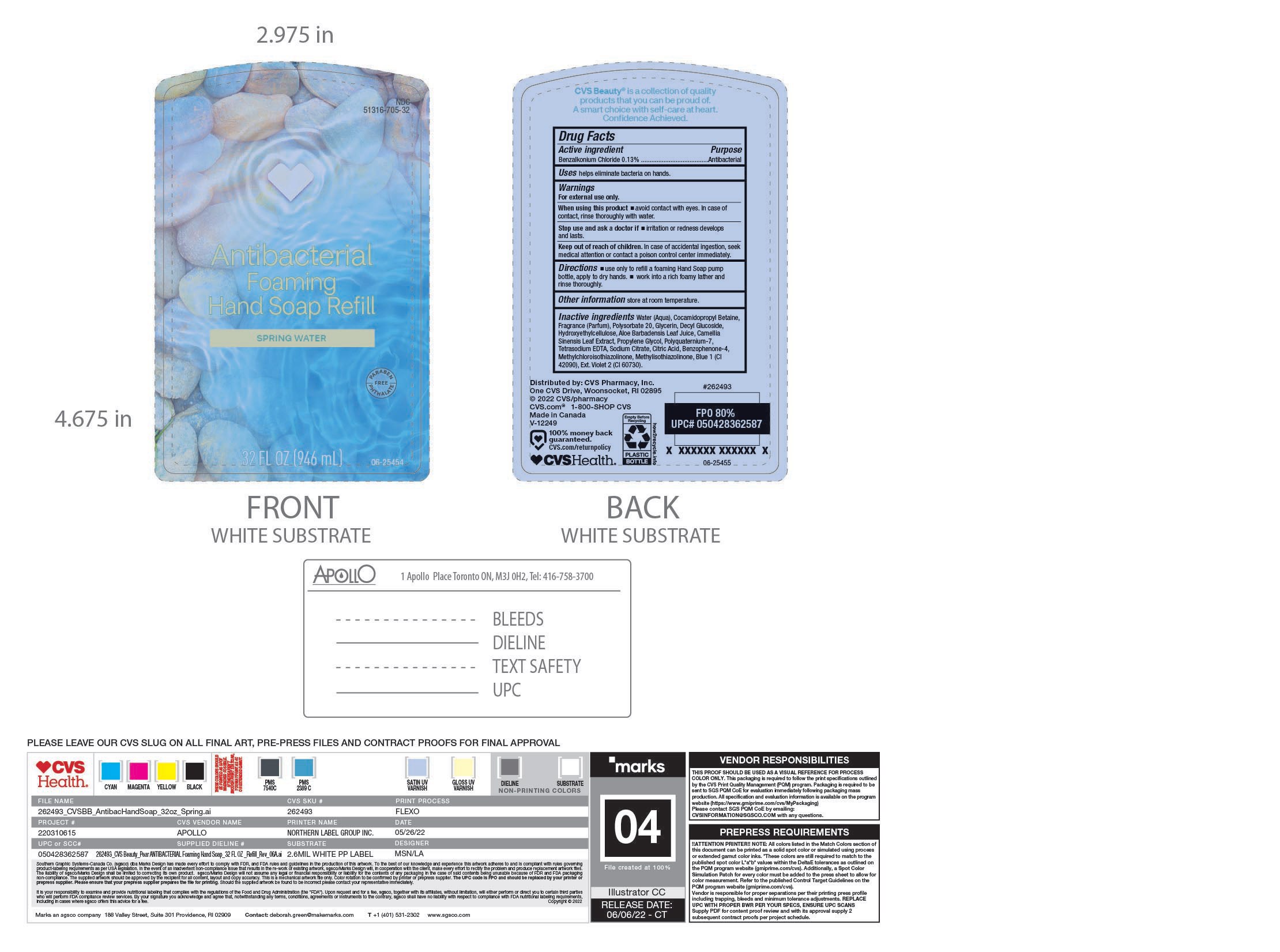 DRUG LABEL: Handsoap
NDC: 51316-705 | Form: SOAP
Manufacturer: CVS Pharmacy Inc.
Category: otc | Type: HUMAN OTC DRUG LABEL
Date: 20241019

ACTIVE INGREDIENTS: BENZALKONIUM CHLORIDE 130 mg/100 mL
INACTIVE INGREDIENTS: WATER; HYDROXYETHYL CELLULOSE, UNSPECIFIED; EDETATE SODIUM; DIRECT BLUE 1; GREEN TEA LEAF; METHYLISOTHIAZOLINONE; SODIUM CITRATE; CITRIC ACID MONOHYDRATE; SULISOBENZONE; METHYLCHLOROISOTHIAZOLINONE; ALOE VERA LEAF; PROPYLENE GLYCOL; GLYCERIN; EXT. D&C VIOLET NO. 2; POLYQUATERNIUM-7 (70/30 ACRYLAMIDE/DADMAC; 1600 KD); COCAMIDOPROPYL BETAINE; FRAGRANCE CLEAN ORC0600327; POLYSORBATE 20; DECYL GLUCOSIDE

NDC 51316-705

ACTIVE INGREDIENT

Benzalkonium Chloride

PURPOSE

Antibacterial- Helps eliminate bacteria on hands.

WARNINGS

For external use only

WHEN USING

Avoid contact with eyes, If this occurs, rinse throughly with water.

Stop use and ask a doctor ifirritation or redness develops and lasts

KEEP OUT OF REACH OF CHILDREN

In case of accidental ingestion, seek medical attention or contact a poison control centre immediately.

DOSAGE AND ADMINISTRATION

Apply onto dry hands, work into a lather, rinse and dry throughly.

STORAGE AND HANDLING

Store at room temperature

INACTIVE INGREDIENT

Water(Aqua), Cocamidopropyl Betaine, Polysorbate 20, Fragrance (Parfum), Glycerin, Decyl Glucoside, Hydroxyethylcellulose, Aloe Barbadensis, Camellia Sinensis Leaf Extract, Propylene Glycol, Polyquaternium-7, Tetrasodium EDTA, Sodium Citrate, Citric Acid, Benzophenone -4, Methylcholoroisothiazolinone, Methylisothiazolinone, Blue 1 (Cl 42090), Ext. Violet 2 (Cl 60730).

INDICATIONS AND USAGE

Helps eliminate bacteria on the skin